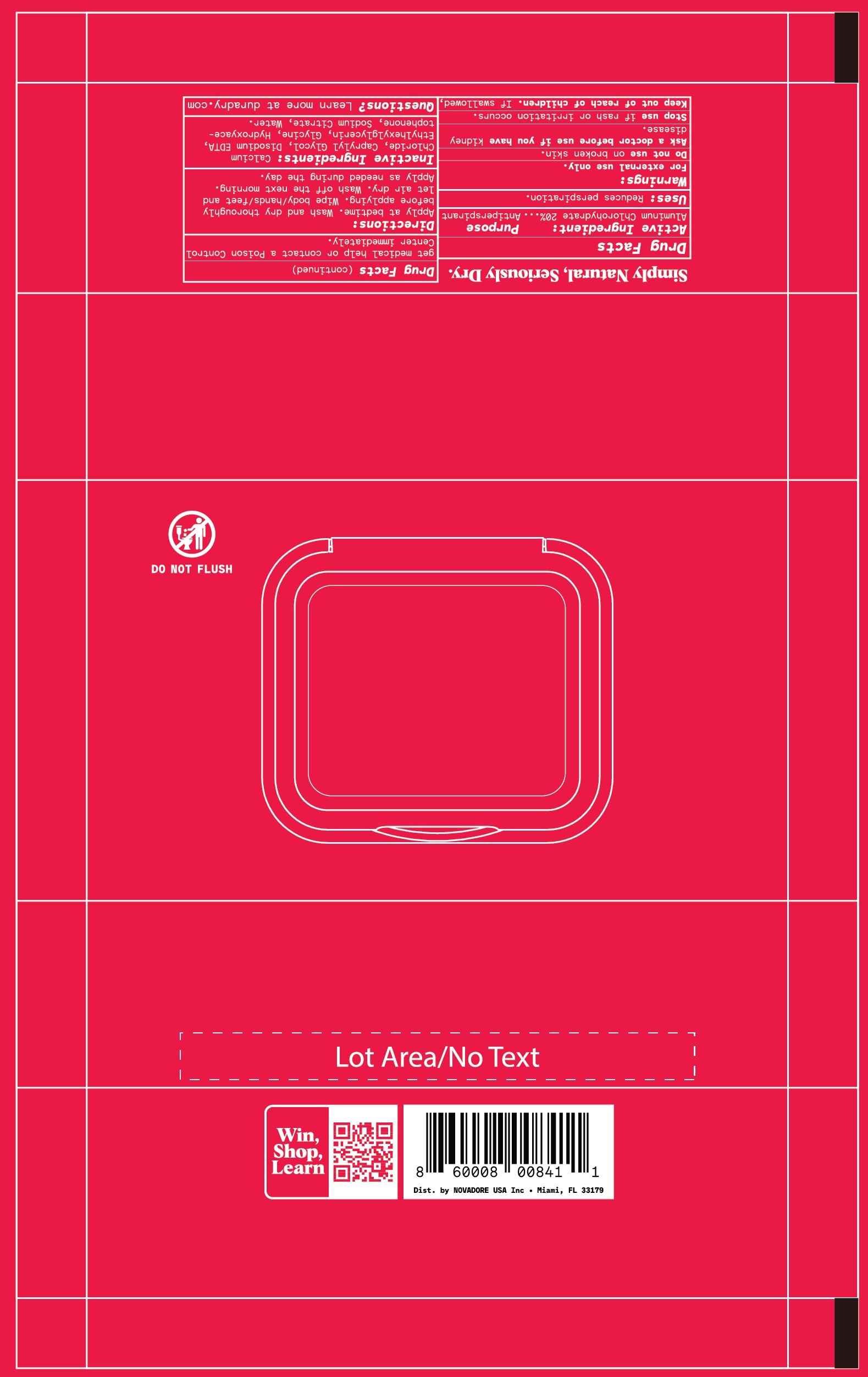 DRUG LABEL: Whole Body Antiperspirant Wipes
NDC: 69990-402 | Form: CLOTH
Manufacturer: Novadore USA Inc
Category: otc | Type: HUMAN OTC DRUG LABEL
Date: 20251110

ACTIVE INGREDIENTS: ALUMINUM CHLOROHYDRATE 200 mg/1 mL
INACTIVE INGREDIENTS: GLYCINE; WATER; EDETATE DISODIUM; SODIUM CITRATE; CAPRYLYL GLYCOL; ETHYLHEXYLGLYCERIN; HYDROXYACETOPHENONE; CALCIUM CHLORIDE

Duradry Antiperspirant Body Wipes

Active Ingredient

Aluminum Chlorohydrate 20%

Purpose

Antiperspirant

Uses

Reduces perspiration

Warnings

For external use only.

Do not use

on broken skin

Ask a doctor before use

if you have kidney disease.

Keep out of reach of children

If swallowed, get medical help or contact a Poison Control Center immediately.

Stop use

if rash or irritation occurs.

Directions

Apply at bedtime. Wash and dry thoroughly before applying. Wipe body/hands/feet and let air dry. Wash off the next morning. Apply as needed during the day.

Inactive ingredients

Calcium Chloride, Caprylyl Glycol, Disodium EDTA, Ethylhexylglycerin, Glycine, Hydroxyacetophenone, Sodium Citrate, Water.

Questions?

Learn more at duradry.com